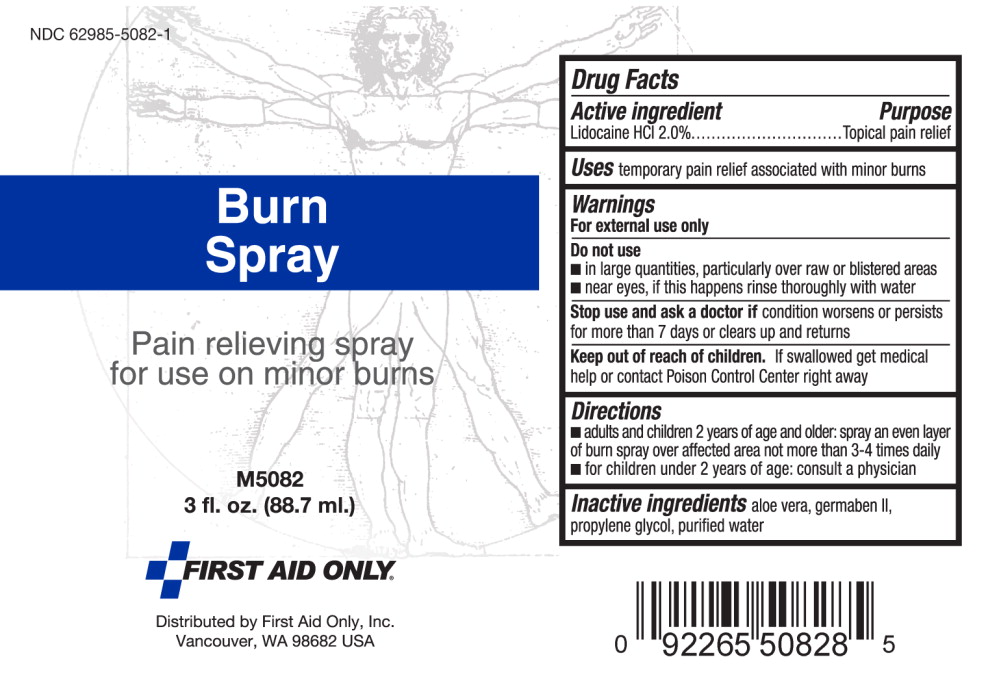 DRUG LABEL: Burn
NDC: 62985-5082 | Form: SPRAY
Manufacturer: First Aid Only, Inc
Category: otc | Type: HUMAN OTC DRUG LABEL
Date: 20140813

ACTIVE INGREDIENTS: Lidocaine Hydrochloride 20 g/1 L
INACTIVE INGREDIENTS: aloe vera leaf; propylene glycol; diazolidinyl urea; water

Drug Facts

Active Ingredients

Lidocaine HCL 2.0%

Purpose

Topical Pain Relief

Uses

temporary pain relief associated with minor burns

Warnings

For external use only.

Do not use

- In large quantities, particularly over raw or blistered area
- Near eyes, if this happens rinse thoroughly with water

Stop use and ask doctor if condition worsens or persists for more than 7 days or clears up and returns

Keep out of reach of children. If swallowed get medical help or contact a Poison Control Center right away.

Directions

- Adults and children 2 years of age and older; spray an even layer of burn spray over affected area not more than 3-4 times daily
- For children under 2 years of age, consult a physician.

Inactive ingredients

aloe vera, germaben II. Propylene glycol, purified water

PACKAGE LABEL

Burn Spray

Pain relieving spray for use on minor burns.

M5082

3 fl. oz. (88.7 ml.)
----------
FIRST AID ONLY

Distributed by First Aid Only, Inc.

Vancouver, WA 96882 USA